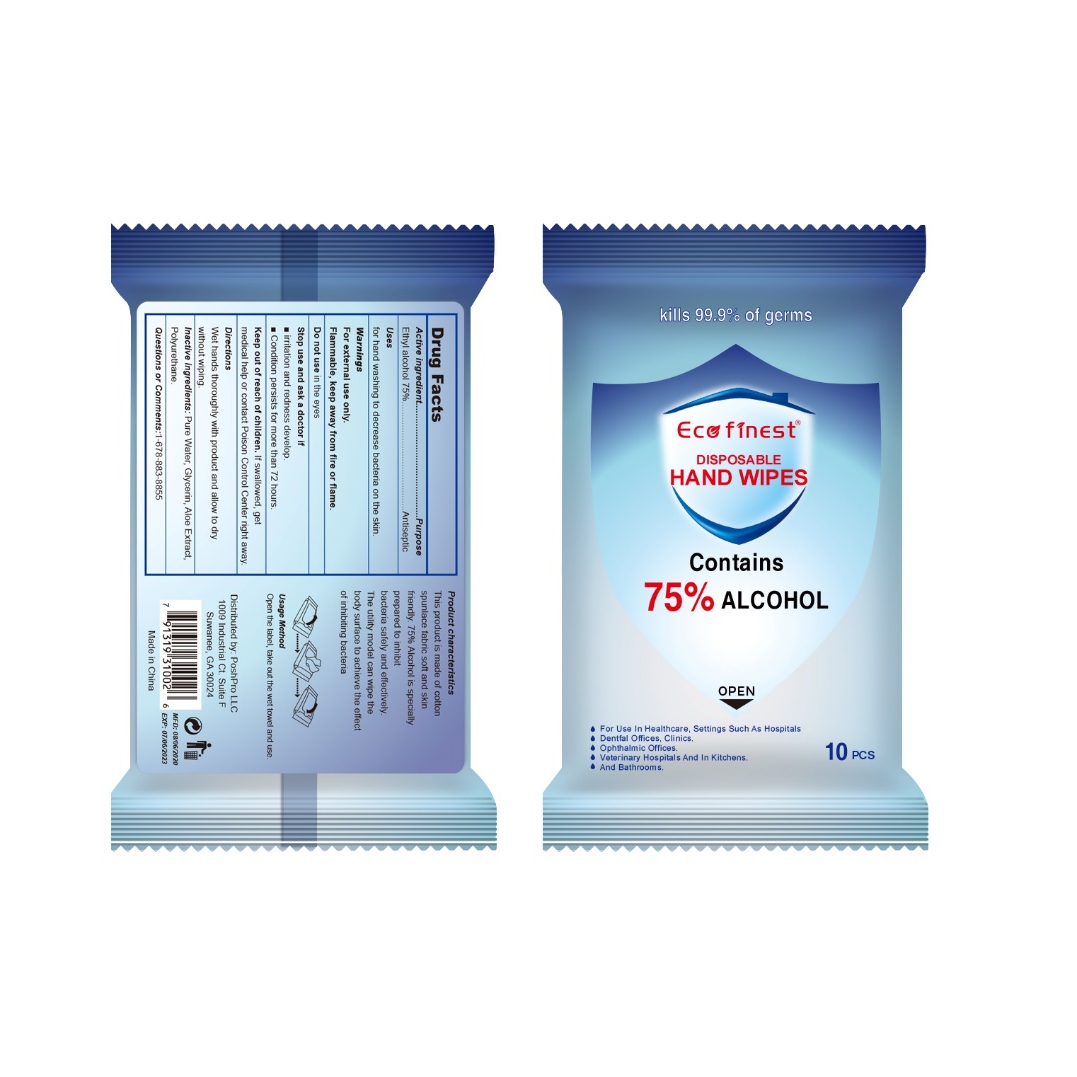 DRUG LABEL: Alcohol Wipes
NDC: 55453-007 | Form: CLOTH
Manufacturer: Guangzhou Yikang Biotechnology Co., Ltd.
Category: otc | Type: HUMAN OTC DRUG LABEL
Date: 20200908

ACTIVE INGREDIENTS: ALCOHOL 15 mL/10 1
INACTIVE INGREDIENTS: GLYCERIN; WATER; POLYURETHANE-34 (40 MPA, TENSILE STRENGTH OF FILM AT BREAK); ALOE

DOSAGE AND ADMINISTRATION

Store in a cool and dry place.

INACTIVE INGREDIENT

Pure Water, Glycerin, Aloe Extract, Polyurethane

INDICATIONS AND USAGE

Wet hands thoroughly with product and allow to dry without wiping.

ACTIVE INGREDIENT

Ethyl Alcohol

keep out of reach of children

PURPOSE

Disinfection

Sterilization
No Rinseing

WARNINGS

For external use only.Flammable, keep away from fire or flame.